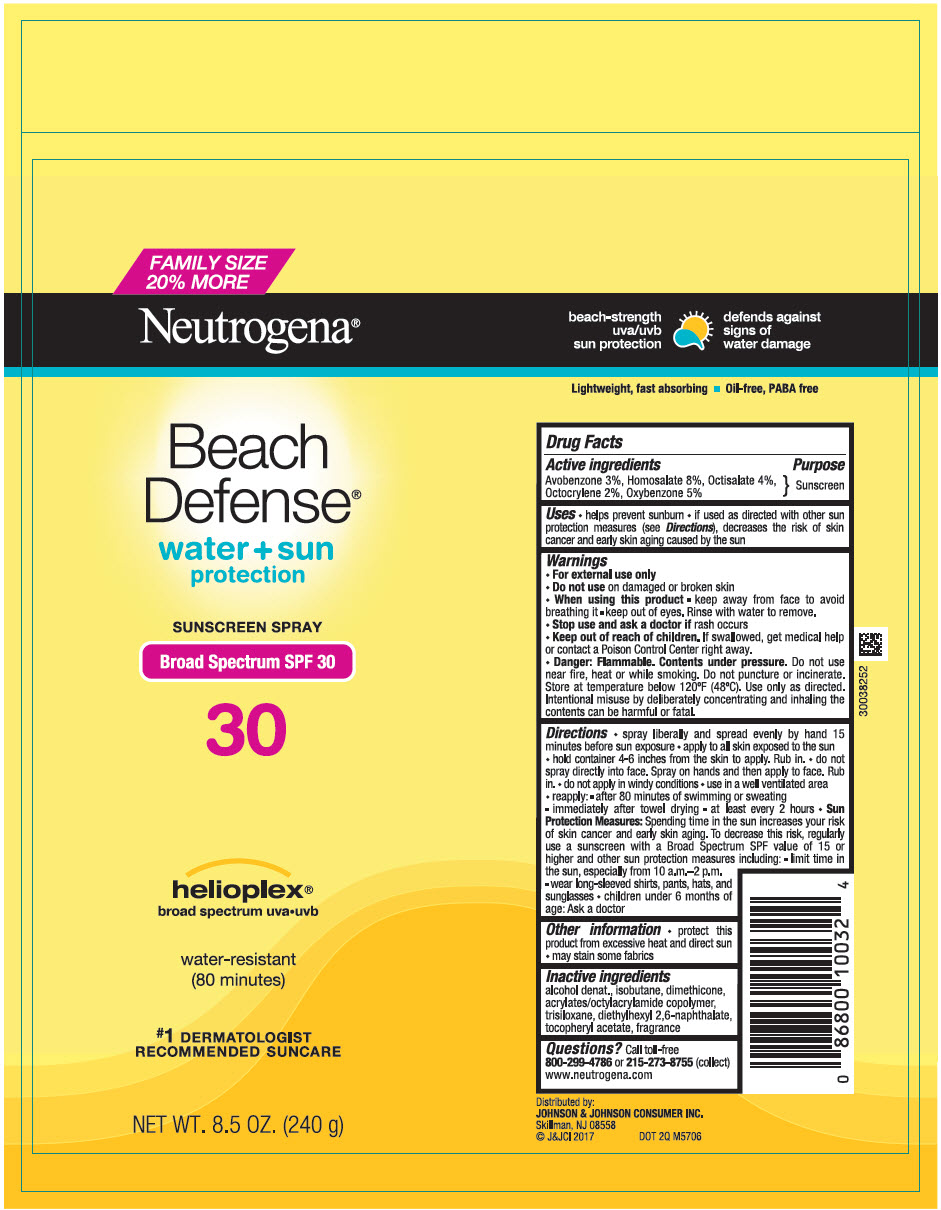 DRUG LABEL: Neutrogena Beach Defense Water Plus Sun Protection
NDC: 69968-0101 | Form: SPRAY
Manufacturer: Kenvue Brands LLC
Category: otc | Type: HUMAN OTC DRUG LABEL
Date: 20250926

ACTIVE INGREDIENTS: HOMOSALATE 30 mg/1 g; AVOBENZONE 30 mg/1 g; OCTISALATE 40 mg/1 g; OCTOCRYLENE 20 mg/1 g; OXYBENZONE 50 mg/1 g
INACTIVE INGREDIENTS: ACRYLATE/ISOBUTYL METHACRYLATE/N-TERT-OCTYLACRYLAMIDE COPOLYMER (75000 MW); ALCOHOL; ISOBUTANE; DIMETHICONE; TRISILOXANE; DIETHYLHEXYL 2,6-NAPHTHALATE; .ALPHA.-TOCOPHEROL ACETATE

Neutrogena® Beach Defense® water+sun protection SUNSCREEN SPRAY Broad Spectrum SPF 30

Drug Facts

Active ingredients

Avobenzone 3%
Homosalate 8%
Octisalate 4%
Octocrylene 2%
Oxybenzone 5%

Purpose

Sunscreen

Uses

- helps prevent sunburn Sunscreen
- If used as directed with other sun protection measures (see Directions), decreases the risk of skin cancer and early skin aging caused by the sun

Warnings

- For external use only

- Do not use on damaged or broken skin

- When using this product
  - keep away from face to avoid breathing it
  - keep out of eyes. Rinse with water to remove

- Stop use and ask a doctor if rash occurs

- Keep out of reach of children. If swallowed, get medical help or contact a Poison Control Center right away.

- Caution: Flammable. Contents under pressure. Do not use near fire, heat or while smoking. Do not puncture or incinerate. Store at temperature below 120°F (48°C). Use only as directed. Intentional misuse by deliberately concentrating and inhaling the contents can be harmful or fatal.

Directions

- spray liberally and spread evenly by hand 15 minutes before sun exposure
- apply to all skin exposed to the sun
- hold container 4-6 inches from the skin to apply. Rub in.
- do not spray directly into face. Spray on hands and then apply to face. Rub in.
- do not apply in windy conditions
- use in a well-ventilated area.
- reapply:
  - after 80 minutes of swimming or sweating
  - immediately after towel drying
  - at least every 2 hours
- Sun Protection Measures. Spending time in the sun increases your risk of skin cancer and early skin aging. To decrease this risk, regularly use a sunscreen with a Broad Spectrum SPF value of 15 or higher and other sun protection measures including:
  - limit time in the sun, especially from 10 a.m.-2 p.m.
  - wear long-sleeved shirts, pants, hats, and sunglasses
- children under 6 months of age: Ask a doctor

Other information

- protect this product from excessive heat and direct sun
- may stain some fabrics

Inactive ingredients

alcohol denat., isobutane, dimethicone, acrylates/octylacrylamide copolymer, trisiloxane, diethylhexyl 2,6 naphthalate, tocopheryl acetate, fragrance

Questions?

Call toll-free 800-299-4786 or 215-273-8755 (collect)
www.neutrogena.com

Distributed by:
JOHNSON & JOHNSON CONSUMER INC.
Skillman, NJ 08558

PRINCIPAL DISPLAY PANEL - 240 g Can Label

FAMILY SIZE
20% MORE

Neutrogena®

Beach
Defense®

water + sun
protection

SUNSCREEN SPRAY

Broad Spectrum SPF30

30

helioplex®
broad spectrum uva-uvb

water resistant
(80 minutes)

#1 DERMATOLOGIST
RECOMMENDED SUNCARE

NET WT. 8.5 OZ. (240g)